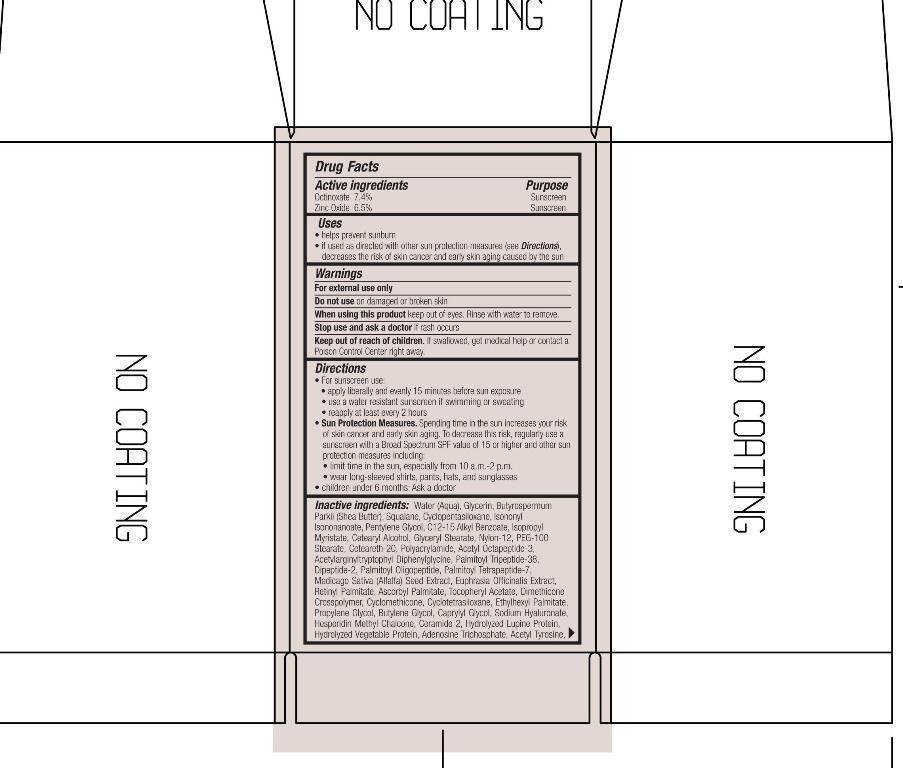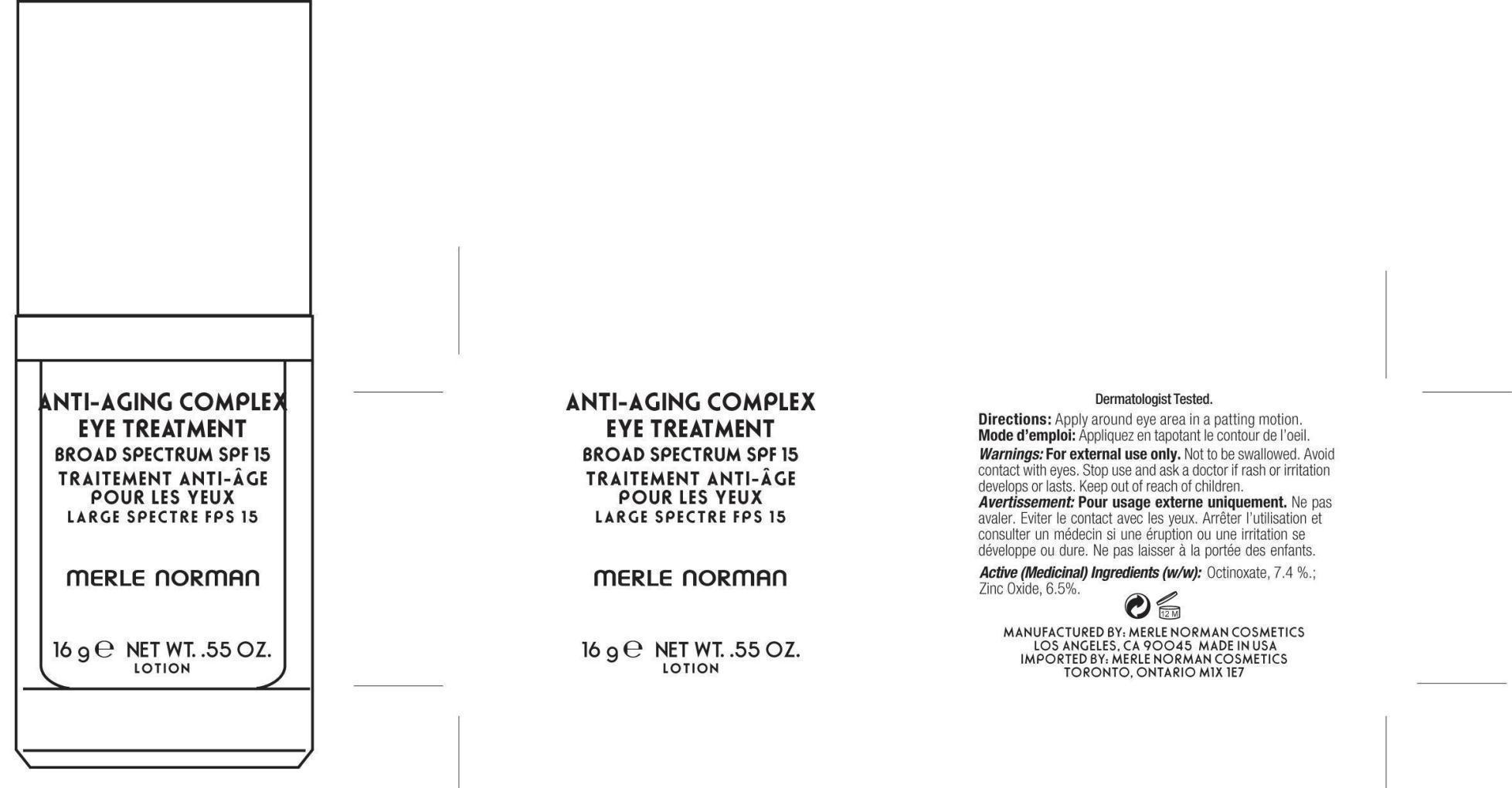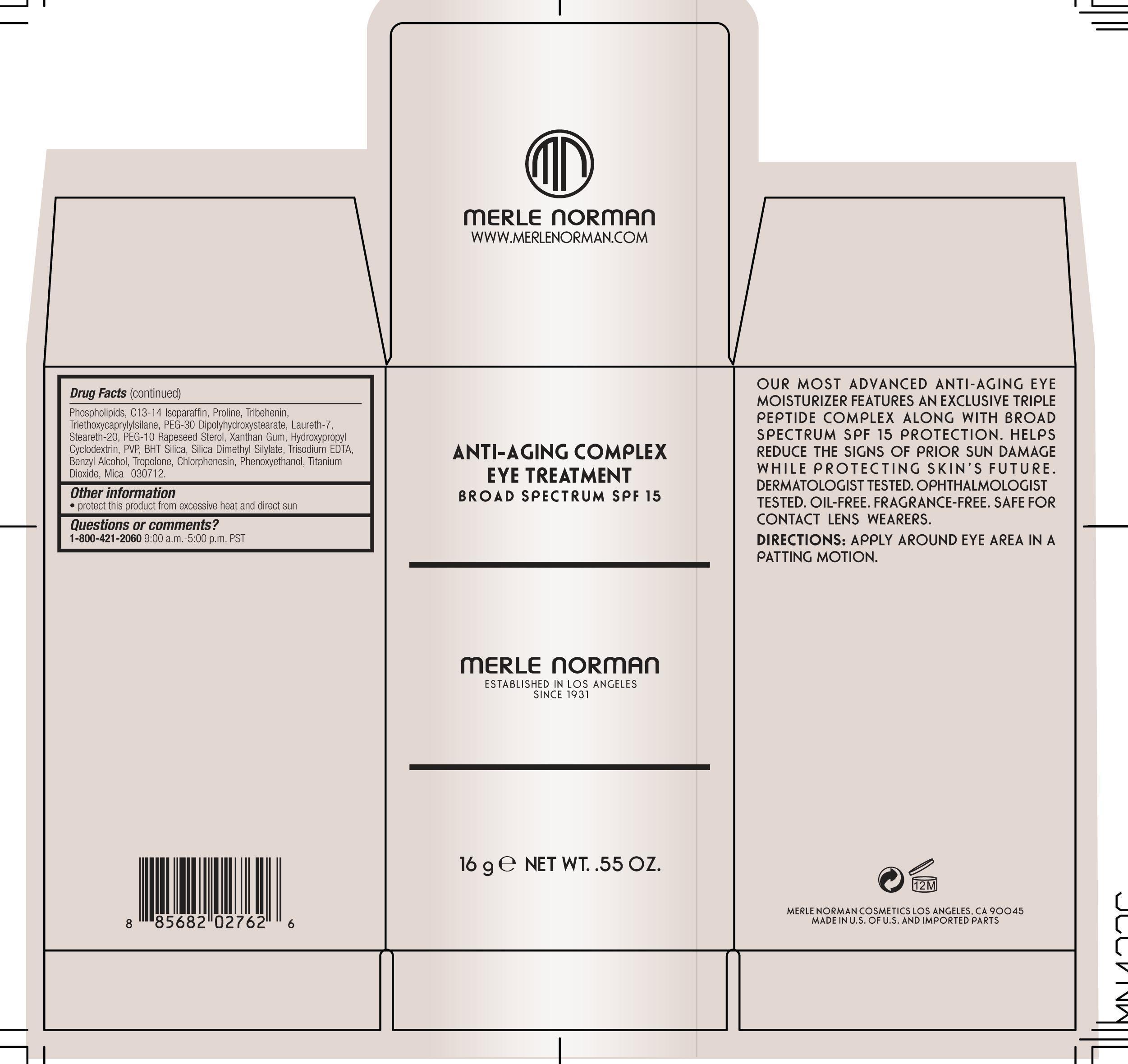 DRUG LABEL: Anti-Aging Complex Eye Treatment
NDC: 57627-150 | Form: LOTION
Manufacturer: Merle Norman Cosmetics, Inc
Category: otc | Type: HUMAN OTC DRUG LABEL
Date: 20251120

ACTIVE INGREDIENTS: OCTINOXATE 1.18 g/16 g; ZINC OXIDE 1.04 g/16 g
INACTIVE INGREDIENTS: VITAMIN A PALMITATE; ASCORBYL PALMITATE; .ALPHA.-TOCOPHEROL ACETATE; CYCLOMETHICONE; CYCLOMETHICONE 4; ETHYLHEXYL PALMITATE; PROPYLENE GLYCOL; BUTYLENE GLYCOL; CAPRYLYL GLYCOL; HYALURONATE SODIUM; HESPERIDIN METHYLCHALCONE; CERAMIDE 2; ADENOSINE TRIPHOSPHATE; N-ACETYLTYROSINE; EGG PHOSPHOLIPIDS; C13-14 ISOPARAFFIN; PROLINE; TRIBEHENIN; TRIETHOXYCAPRYLYLSILANE; PEG-30 DIPOLYHYDROXYSTEARATE; LAURETH-7; STEARETH-20; PEG-10 RAPESEED STEROL; XANTHAN GUM; BUTYLATED HYDROXYTOLUENE; SILICON DIOXIDE; SILICA DIMETHYL SILYLATE; EDETATE TRISODIUM; BENZYL ALCOHOL; TROPOLONE; CHLORPHENESIN; PHENOXYETHANOL; TITANIUM DIOXIDE; MICA; GLYCERIN; SHEA BUTTER; SQUALANE; CYCLOMETHICONE 5; ISONONYL ISONONANOATE; PENTYLENE GLYCOL; ALKYL (C12-15) BENZOATE; ISOPROPYL MYRISTATE; CETOSTEARYL ALCOHOL; GLYCERYL MONOSTEARATE; NYLON-12; PEG-100 STEARATE; POLYOXYL 20 CETOSTEARYL ETHER; POLYACRYLAMIDE (1500 MW); ACETYL OCTAPEPTIDE-3; VALYLTRYPTOPHAN; PALMITOYL OLIGOPEPTIDE; PALMITOYL TETRAPEPTIDE-7; ALFALFA SEED; EUPHRASIA STRICTA; WATER

Anti-Aging Complex Eye Treatment Broad Spectrum SPF 15

Active ingredients Purpose

Octinoxate 7.4% Sunscreen

Zinc Oxide 6.5% Sunscreen

Uses

helps prevent sunburn

If used as directed with other sun protection measures (See Directions) decreases the risk of skin cancer and early skin aging caused by the sun.

Keep out of reach of children. If swallowed, get medical help or contact a Poison Control Center right away.

Stop use and ask a doctor if rash occurs

Warnings

For External use only

Do not use on damaged or broken skin

When using this product keep out of eyes. Rinse with water to remove.

Directions

For sunscreen

- apply liberally and evenly 15 minutes before sun exposure

- use a water resistant sunscreen if swimming

- reapply at least every 2 hours

Sun Protection Measures. Spending time in the sun increase your risk of skin cancer and early skin aging. To decrease this risk of skin cancer, regularly use a sunscreen with a Broad Spectrum SPF value of 15 or higher and other sun protection measures including"

- limit time in the sun, especially from 10 a.m.-2p.m.

- wear long-sleeved shirts, pants, hats, and sunglasses

children under six months: Ask a doctor

Inactive ingredients

Water (Aqua), Glycerin, Butyrospermum Parkii (Shea Butter), Squalane, Cyclopentasiloxane, Isononyl Myristate, Pentylene Glycol,
C12-15 Alkyl Benzoate, Isopropyl Myristate, Cetearyl Alcohol, Glyceryl Stearate, Nylon-12, PEG-100 Stearate, Ceteareth-20, Polyacrylamide,
Acetyl Octapeptide-3, Acetylarginyltryptophyl Diphenylglycine, Palmitoyl Tetrapeptide-7, Medicago Sativa (Alfafa) Seed Extract,
Euphrasia Officinalis Extract, Retinyl Palmitate, Ascorbyl Palmitate, Tocopheryl Acetate, Dimethicone Crosspolymer, Cyclomethicone,
Cyclotetrasiloxane, Ethylhexyl palmitate, Propylene Glycol, Butylene Glycol, Caprylyl Glycol, Sodium Hyaluronate, Hesperidin Methyl Chalcone, Ceramide-2, Hydrolyzed Lupine Protein, Hydrolyzed Vegetable Protein, Adenosine Triphosphate, Acetyl Tyrosine, Phospholipids, C13-14 Isoparaffin, Proline, Tribehenin, Triethoxycaprylylsilane, PEG-30 Dipolyhydroxypropyl, Laureth-7, Steareth-20 PEG-10 Rapeseed Sterol, Xanthan Gum, Hydroxypropyl Cyclodextrin, PVP, BHT Silica, Silica Dimethyl Silylate, Trisodium EDTA, Benzyl Alcohol, Tropolone Chlorphenesin, Phenoxyethanol, Titanium Dioxide, Mica.

PACKAGE LABEL

Anti-Aging Complex Eye Treatment

Broad Spectrum

Merle Norman

established in Los Angeles since 1931

16 g Net Wt. .55 oz